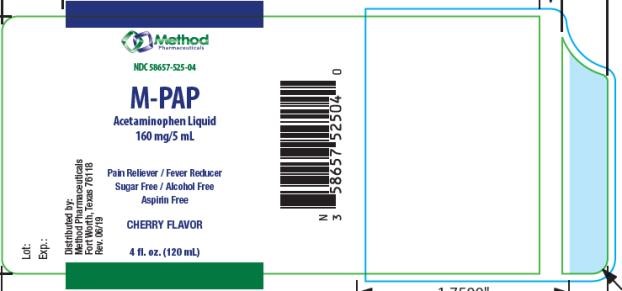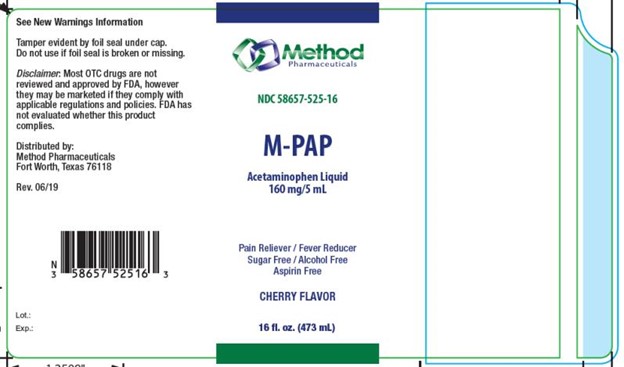 DRUG LABEL: M-PAP
NDC: 58657-525 | Form: LIQUID
Manufacturer: Method Pharmaceuticals, LLC
Category: otc | Type: HUMAN OTC DRUG LABEL
Date: 20251021

ACTIVE INGREDIENTS: ACETAMINOPHEN 160 mg/5 mL
INACTIVE INGREDIENTS: CITRIC ACID MONOHYDRATE; FD&C RED NO. 40; GLYCERIN; POLYETHYLENE GLYCOL, UNSPECIFIED; WATER; SODIUM BENZOATE; TRISODIUM CITRATE DIHYDRATE; SACCHARIN SODIUM; SORBITOL

M-PAP

M-PAP

Acetaminophen Liquid

160 mg/5 mL

Pain Reliever / Fever Reducer

Sugar Free / Alcohol Free

Aspirin Free

CHERRY FLAVOR

Drug Facts

Active ingredient

(in each 5 mL teaspoonful)

Acetaminophen, USP 160 mg ....................

Purpose

Pain reliever/fever reducer

Uses

temporarily relieves minor aches and pains due to:

- Headache
- muscular aches
- backache
- arthritis
- the common cold
- toothache
- menstrual cramps
- reduces fever

Warnings

Liver Warning: This product contains acetaminophen. Severe liver damage may occur if you take:

- more than 8 teaspoonfuls (40 mL) in 24 hours, which is the maximum daily amount
- with other drugs containing acetaminophen
- 3 or more alcoholic drinks every day while using this product

Allergy alert: Acetaminophen may cause severe skin reactions. Symptoms may include:

- skin reddening
- blisters
- rash

If a skin reaction occurs, stop use and seek medical help right away.

Ask a doctor before use

if you have health issues especially liver disease.

Ask a doctor or pharmacist before use

if you are taking other drugs, including the blood thinner warfarin.

Do not use

with any other drug containing acetaminophen (prescription or nonprescription). If you are not sure whether a drug contains acetaminophen, ask a doctor or pharmacist.

- for more than 10 days for pain unless directed by a doctor
- for more than 3 days for fever unless directed by a doctor
- if you are allergic to acetaminophen or any of the inactive ingredients in this product.

Stop use and ask a doctor if

- new symptoms occur such as rash, hives, itching or hoarseness
- redness or swelling is present
- pain gets worse or lasts for more than 10 days
- fever gets worse or lasts for more than 3 days
- symptoms do not improve

These could be signs of a serious condition.

If pregnant or breast-feeding,

ask a health professional before use.

Keep out of reach of children.

In case of overdose, get medical help or contact a Poison Control Center right away. Prompt medical attention is critical even if you do not notice any signs or symptoms.

Directions

Do not exceed recommended dosage.

Overdose Warnings: Taking more than the recommended dose (overdose) can cause serious health problems, including liver damage.

- adults and children 12 years of age and older: take 2 teaspoonfuls (10 mL) every 6 hours; do not exceed

8 teaspoonfuls (40 mL) in 24 hours

- children under 12 years of age: Under the direct guidance of a licensed professional, doctor, or pharmacist.

Other Information

If dispensed, dispense in a tight, light resistant container with a child-resistant cap.

Store at 20°C to 25°C (68°F to 77°F), excursions permitted between 15°C and 30°C (between 59°F and 86°F)

Inactive Ingredients

Bitter Mask, Cherry Flavor, Citric Acid, FD&C Red No. 40, Glycerin, Polyethylene Glycol, Purified Water, Sodium Benzoate, Sodium Citrate Dihydrate, Sodium Saccharin, Sorbitol.

Questions?

1-877-250-3427 M-F (8 a.m. to 5 p.m. CST), or directly to Medwatch at 1-800-332-1088.

Serious side effects associated with use of this product may be reported to this number.

See New Warnings Information

Tamper evident by foil seal under cap.

Do not use if foil seal is broken or missing.

Disclaimer: Most OTC drugs are not reviewed and approved by FDA, however they may be marketed if they comply with applicable regulations and policies. FDA has not evaluated whether this product complies.

Distributed by:

Method Pharmaceuticals

Fort Worth, Texas 76118

Rev. 06/19

PRINCIPAL DISPLAY PANEL

NDC 58657-525-04
M-PAP
Acetaminophen Liquid
160 mg/5 mL
Cherry Flavor
4 fl. oz. (120 mL)

PRINCIPAL DISPLAY PANEL

NDC 58657-525-16
M-PAP
Acetaminophen Liquid
160 mg/5 mL
Cherry Flavor
16 fl. oz. (473 mL)